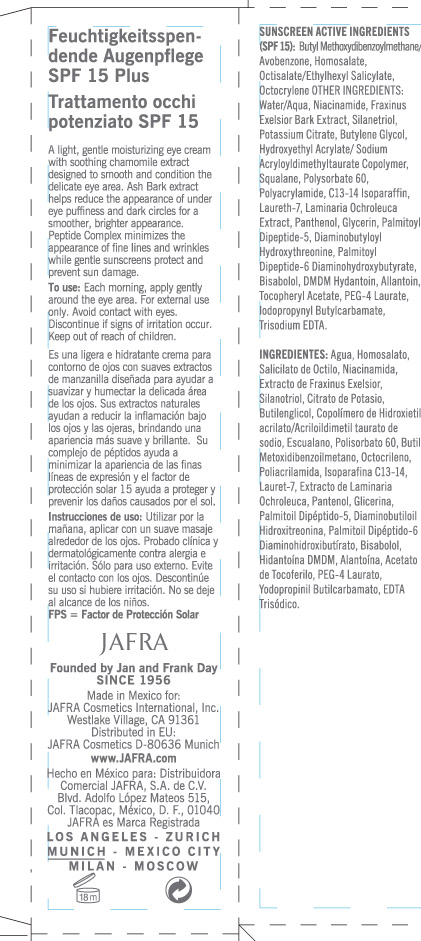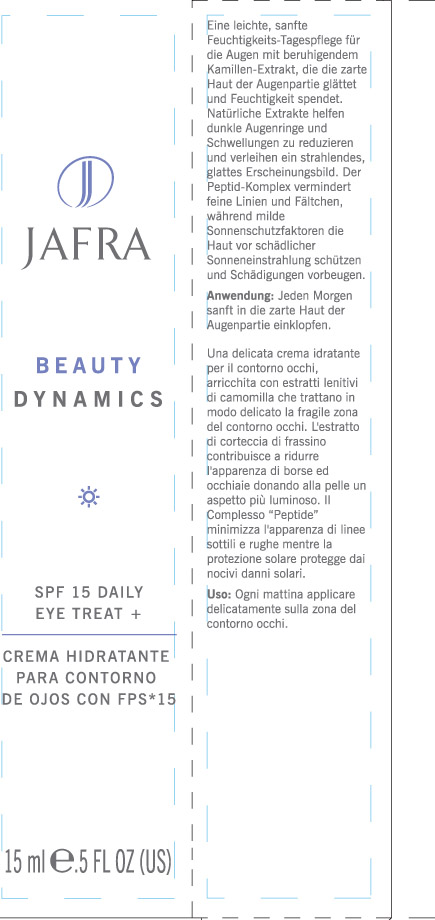 DRUG LABEL: Beauty Dynamics
NDC: 68828-072 | Form: CREAM
Manufacturer: JAFRA COSMETICS INTERNATIONAL
Category: otc | Type: HUMAN OTC DRUG LABEL
Date: 20120518

ACTIVE INGREDIENTS: AVOBENZONE 2.5 mL/100 mL; HOMOSALATE 7.5 mL/100 mL; OCTISALATE 5 mL/100 mL; OCTOCRYLENE 1.75 mL/100 mL
INACTIVE INGREDIENTS: WATER; NIACINAMIDE; FRAXINUS EXCELSIOR BARK; SILANETRIOL; POTASSIUM CITRATE; BUTYLENE GLYCOL; HYDROXYETHYL ACRYLATE/SODIUM ACRYLOYLDIMETHYL TAURATE COPOLYMER (45000 MPA.S AT 1%); POLYSORBATE 60; POLYACRYLAMIDE (1500 MW); C13-14 ISOPARAFFIN; LAURETH-7; LAMINARIA OCHROLEUCA; PANTHENOL; GLYCERIN; LEVOMENOL; DMDM HYDANTOIN; ALLANTOIN; .ALPHA.-TOCOPHEROL ACETATE; PEG-4 LAURATE; IODOPROPYNYL BUTYLCARBAMATE; EDETATE TRISODIUM

Beauty Dynamics SPF 15 Daily Eye Treat +

ACTIVE INGREDIENT

Sunscreen Active Ingredients (SPF 15): Butyl methoxydibenzoylmethane/Avobenzene, Homosalate, Octisalate/Ethylhexyl Salicylate, Octocrylene

Purpose: Sunscreen

Keep out of reach of children

INDICATIONS AND USAGE

Discontinue if signs of irritation occur.

WARNINGS

For external use only. Avoid contact with eyes

DOSAGE AND ADMINISTRATION

To use:

Each morning, apply gently around the eye area.

INACTIVE INGREDIENT

Water/Aqua, Niacinamide, Fraxinus Exelsior Bark Extract, Silanetriol, Potassium Citrate, Butylene Glycol, Hydroxyethyl Acrylate/Sodium Acryloyldimethyltaurate Copolymer, Squalane, Polysorbate 60, Polyacrylamide, C13-14 Isoparaffin, Laureth-7, Laminaria Ochroleuca Extract, Panthenol, Glycerin, Palmitoyl Dipeptide-5, Diaminobutyloyl Hydroxythreonine, Palmitoyl Dipeptide-6 Diaminohydroxybutyrate, Bisabolol, DMDM Hydantoin, Allantoin, Tocopheryl Acetate, PEG-4 Laurate, Iodopropynyl Butylcarbamate, Trisodium EDTA.

PACKAGE LABEL

Jafra

Beauty Dynamics
SPF 15 Daily Eye Treat +
Crema Hidratante
Para Contorno
De Ojos con FPS*15
15 ml .5 Fl Oz (US)